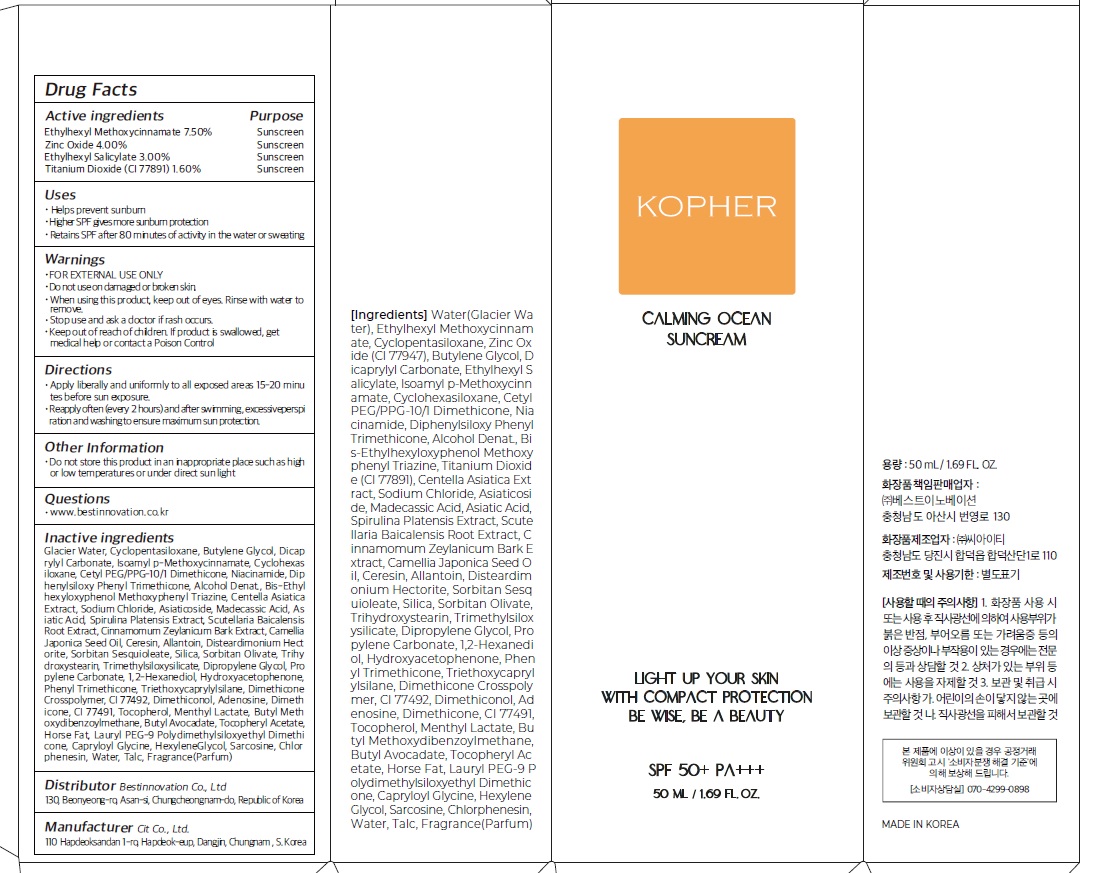 DRUG LABEL: Kopher Calming Ocean Sun
NDC: 83069-010 | Form: CREAM
Manufacturer: Best Innovation
Category: otc | Type: HUMAN OTC DRUG LABEL
Date: 20221027

ACTIVE INGREDIENTS: OCTINOXATE 7.50 g/100 mL; Zinc Oxide 4.0 g/100 mL; OCTISALATE 3.0 g/100 mL; Titanium Dioxide 1.60 g/100 mL
INACTIVE INGREDIENTS: Water; CYCLOMETHICONE 5; Butylene Glycol

ACTIVE INGREDIENTS

Ethylhexyl Methoxycinnamate 7.50%
Zinc Oxide 4.00%
Ethylhexyl Salicylate 3.00%
Titanium Dioxide (CI 77891) 1.60%

INACTIVE INGREDIENTS

Glacier Water, Cyclopentasiloxane, Butylene Glycol, Dicaprylyl Carbonate, Isoamyl p-Methoxycinnamate, Cyclohexasiloxane, Cetyl PEG/PPG-10/1 Dimethicone, Niacinamide, Diphenylsiloxy Phenyl Trimethicone, Alcohol Denat., Bis-Ethylhexyloxyphenol Methoxyphenyl Triazine, Centella Asiatica Extract, Sodium Chloride, Asiaticoside, Madecassic Acid, Asiatic Acid, Spirulina Platensis Extract, Scutellaria Baicalensis Root Extract, Cinnamomum Zeylanicum Bark Extract, Camellia Japonica Seed Oil, Ceresin, Allantoin, Disteardimonium Hectorite, Sorbitan Sesquioleate, Silica, Sorbitan Olivate, Trihydroxystearin, Trimethylsiloxysilicate, Dipropylene Glycol, Propylene Carbonate, 1,2-Hexanediol, Hydroxyacetophenone, Phenyl Trimethicone, Triethoxycaprylylsilane, Dimethicone Crosspolymer, CI 77492, Dimethiconol, Adenosine, Dimethicone, CI 77491, Tocopherol, Menthyl Lactate, Butyl Methoxydibenzoylmethane, Butyl Avocadate, Tocopheryl Acetate, Horse Fat, Lauryl PEG-9 Polydimethylsiloxyethyl Dimethicone, Capryloyl Glycine, Hexylene Glycol, Sarcosine, Chlorphenesin, Water, Talc, Fragrance(Parfum)

PURPOSE

Sunscreen

WARNINGS

■ FOR EXTERNAL USE ONLY
■ Do not use on damaged or broken skin.
■ When using this product, keep out of eyes. Rinse with water to remove.
■ Stop use and ask a doctor if rash occurs.
■ Keep out of reach of children. If product is swallowed, get medical help or contact a Poison Control

Keep out of reach of children. If product is swallowed, get medical help or contact a Poison Control

Uses

■ Helps prevent sunburn
■ Higher SPF gives more sunburn protection
■ Retains SPF after 80 minutes of activity in the water or sweating

Directions

■ Apply liberally and uniformly to all exposed areas 15-20 minutes before sun exposure.
■ Reapply often (every 2 hours) and after swimming, excessive perspiration and washing to ensure maximum sun protection.

Other Information

■ Do not store this product in an inappropriate place such as high or low temperatures or under direct sun light

Questions

■ www.bestinnovation.co.kr